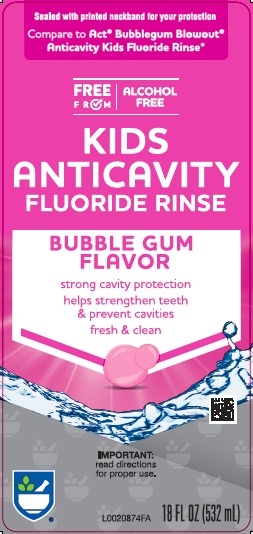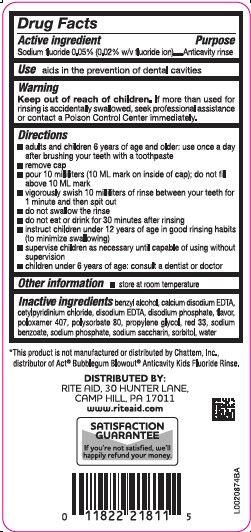 DRUG LABEL: Anticavity Rinse
NDC: 11822-4004 | Form: MOUTHWASH
Manufacturer: Rite Aid Corporation
Category: otc | Type: HUMAN OTC DRUG LABEL
Date: 20260130

ACTIVE INGREDIENTS: SODIUM FLUORIDE 0.5 mg/1 mL
INACTIVE INGREDIENTS: BENZYL ALCOHOL; EDETATE CALCIUM DISODIUM ANHYDROUS; CETYLPYRIDINIUM CHLORIDE; EDETATE DISODIUM ANHYDROUS; SODIUM PHOSPHATE, DIBASIC, ANHYDROUS; POLOXAMER 407; POLYSORBATE 80; PROPYLENE GLYCOL; D&C RED NO. 33; SODIUM BENZOATE; SODIUM PHOSPHATE; SACCHARIN; SORBITOL; WATER

Rite Aid 004.002/004AE
Anticavity Fluoride Rinse, Bubble Gum

Active ingredient

Sodium fluoride 0.05% (0.02% w/v fluoride ion)

Purpose

Anticavity rinse

Use

aids in the prevention of dental cavities

Warning

for this product

Keep out of reach of children.

If more than used for rinsing is accidentally swallowed, seek professional assistance or contact a Poison Control Center immediately.

Directions

- adults and children 6 years of age and older: use once a day after brushing your teeth with a toothpaste
- remove cap
- pour 10 milliliters (10 ML mark on inside of cap); do not fill above 10 ML mark
- vigorously swish 10 milliliters of rinse between your teeth for 1 minute and then spit out
- do not swallow the rinse
- do not eat or drink for 30 minutes after rinsing
- instruct children under 12 years of age in good rinsing habits (to minimize swallowing)
- supervise children as necessary until capable of using without supervision
- children under 6 years of age: consult a dentist or doctor

Other information

- store at room temperature

Inactive ingredients

benzyl alcohol, calcium disodium EDTA, cetylpyridinium chloride, disodium EDTA, disodium phosphate, flavor, poloxamer 407, polysorbate 80, propylene glycol, red 33, sodium benzoate, sodium phosphate, sodium saccharin, sorbitol, water

Disclaimer

*This product is not manufactured or distributed by Chattem, Inc., distributor of Act®Bubblegum BlowoutAnticavity Kids Fluoride Rinse.

ADVERSE REACTION

Distributed by:

Rite Aid, 30 Hunter Lane,

Camp Hill, PA 170111

www.riteaid.com

SATISFACTION GUARANTEE

If you're not satisfied, we'll happily refund your money.

Principal Panel Display

Sealed with printed neckband for your protection

Compare to Act®Bubblegum Blowout®Anticavity Kids Fluoride Rinse*

Free From

Alcohol Free

Kids Anticavity

Fluoride Rinse

Bubble Gum Flavor

strong cavity protection

helps strengthen teeth & prevent cavities

fresh & clean

Important: read directions for proper use.

18 FL OZ (532 mL)